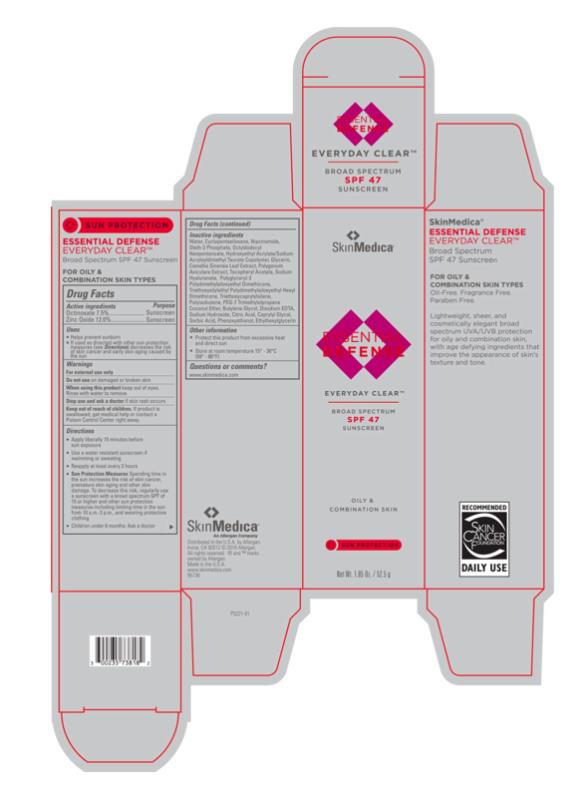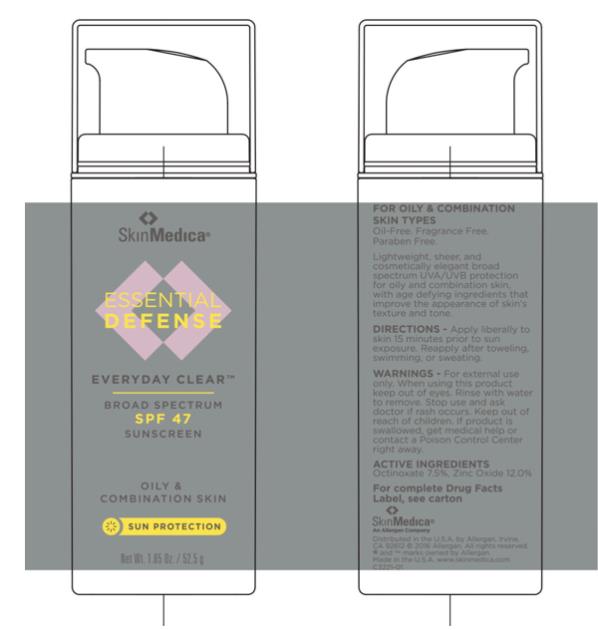 DRUG LABEL: Essential Defense Everyday Clear Broad Spectrum SPF 47 Sunscreen
NDC: 0023-5738 | Form: LOTION
Manufacturer: Allergan, Inc.
Category: otc | Type: HUMAN OTC DRUG LABEL
Date: 20160302

ACTIVE INGREDIENTS: ZINC OXIDE 120 mg/1 g; OCTINOXATE 75 mg/1 g
INACTIVE INGREDIENTS: WATER; CYCLOMETHICONE 5; NIACINAMIDE; OLETH-3 PHOSPHATE; OCTYLDODECYL NEOPENTANOATE; HYDROXYETHYL ACRYLATE/SODIUM ACRYLOYLDIMETHYL TAURATE COPOLYMER (100000 MPA.S AT 1.5%); GLYCERIN; PHENOXYETHANOL; POLYGLYCERYL-3 POLYDIMETHYLSILOXYETHYL DIMETHICONE (4000 MPA.S); POLYISOBUTYLENE (1300 MW); BUTYLENE GLYCOL; .ALPHA.-TOCOPHEROL ACETATE, D-; ETHYLHEXYLGLYCERIN; GREEN TEA LEAF; EDETATE DISODIUM; TRIETHOXYCAPRYLYLSILANE; CAPRYLYL GLYCOL; POLYGONUM AVICULARE TOP; SODIUM HYDROXIDE; CITRIC ACID MONOHYDRATE; SORBIC ACID; HYALURONATE SODIUM

ESSENTIAL DEFENSE EVERYDAY CLEAR BROAD SPECTRUM SPF 47 SUNSCREEN- zinc oxide and octinoxate lotion
Allergan, Inc.
Drug Facts

Active ingredients

Octinoxate 7.5%

Zinc Oxide 12.0%

Purpose

Sunscreen

Sunscreen

Uses

- Helps prevent sunburn
- If used as directed with other sun protection measures (see Directions) decreases the risk of skin cancer and early skin aging caused by the sun

Warnings

For external use only

Do not use

on damaged or broken skin

When using this product

keep out of eyes. Rinse with water to remove.

Stop use and ask a doctor

if skin rash occurs

Keep out of reach of children.

If product is swallowed, get medical help or contact a Poison Control Center right away.

Directions

- Apply liberally 15 minutes before sun exposure
- Use a water resistant sunscreen if swimming or sweating
- Reapply at least every 2 hours
- Sun Protection Measures Spending time in the sun increases the risk of skin cancer, premature skin aging and other skin damage. To decrease this risk, regularly use a sunscreen with a broad spectrum SPF of 15 or higher and other sun protection measures including limiting time in the sun from 10 a.m.-2 p.m., and wearing protective clothing
- Children under 6 months: Ask a doctor

Inactive ingredients

Water, Cyclopentasiloxane, Niacinamide, Oleth-3 Phosphate, Octyldodecyl Neopentanoate, Hydroxyethyl Acrylate/Sodium Acryloyldimethyl Taurate Copolymer, Glycerin, Camellia Sinensis Leaf Extract, Polygonum Aviculare Extract, Tocopheryl Acetate, Sodium Hyaluronate, Polyglyceryl-3 Polydimethylsiloxyethyl Dimethicone, Triethoxysilylethyl Polydimethylsiloxyethyl Hexyl Dimethicone, Triethoxycaprylylsilane, Polyisobutene, PEG-7 Trimethylolpropane Coconut Ether, Butylene Glycol, Disodium EDTA, Sodium Hydroxide, Citric Acid, Caprylyl Glycol, Sorbic Acid, Phenoxyethanol, Ethylhexylglycerin

Other information

- Protect this product from excessive heat and direct sun
- Store at room temperature 15° - 30°C (59° - 86°F)

Questions or comments?

www.skinmedica.com

Principal Display Panel - Carton Label

SkinMedica®
ESSENTIAL
DEFENSE
EVERYDAY CLEAR™
BROAD SPECTRUM
SPF 47
SUNSCREEN
OILY &
COMBINATION SKIN
SUN PROTECTION
Net Wt. 1.85 Oz. / 52.5 g

Principal Display Panel - Tube Label

SkinMedica®
ESSENTIAL
DEFENSE
EVERYDAY CLEAR™
BROAD SPECTRUM
SPF 47
SUNSCREEN
OILY &
COMBINATION SKIN
SUN PROTECTION
Net Wt. 1.85 Oz. / 52.5 g